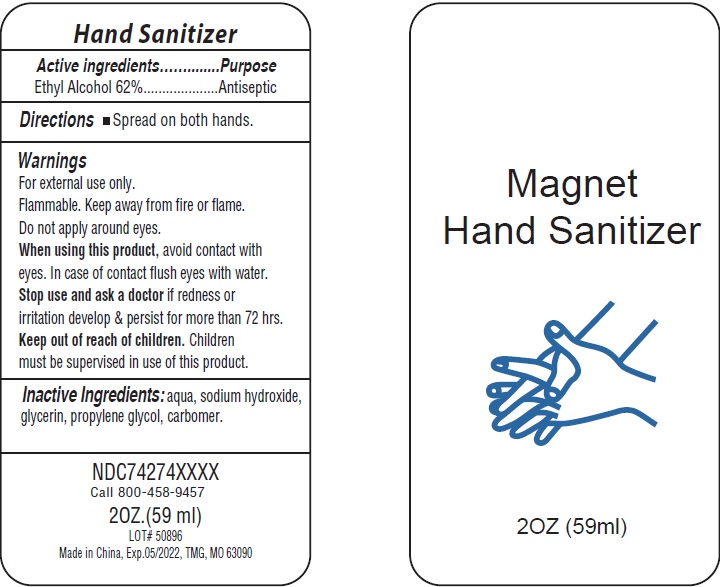 DRUG LABEL: Magnet Hand Sanitizer
NDC: 74274-010 | Form: SOLUTION
Manufacturer: Huizhou Bliss Commodity Co., Ltd
Category: otc | Type: HUMAN OTC DRUG LABEL
Date: 20200424

ACTIVE INGREDIENTS: ALCOHOL 62 mL/100 mL
INACTIVE INGREDIENTS: WATER; CARBOMER INTERPOLYMER TYPE A (ALLYL SUCROSE CROSSLINKED); GLYCERIN; PROPYLENE GLYCOL; SODIUM HYDROXIDE

Active ingredient

Ethyl Alcohol 62%

Purpose

Antiseptic

Use

For hand-washing to decrease bacteria on the skin, only when water is not available.

KEEP OUT OF REACH OF CHILDREN

if swallowed, get medical help or contact a Poison Control Center right away.

Children must be supervised in use of this product.

warnings:

Flamable, keep away from fire and flames

For external use only

Do not apply around eyes.

When using this product, avoid contact with eyes. In case of contact, flush eyes with water.

Stop use and ask a doctor if irritation develop and persist for more than 72 hrs.

Directions

- Spread on both hands.

Inactive ingredients

aqua, sodium hydroxide, glycerin, propyene glycol, carbomer.